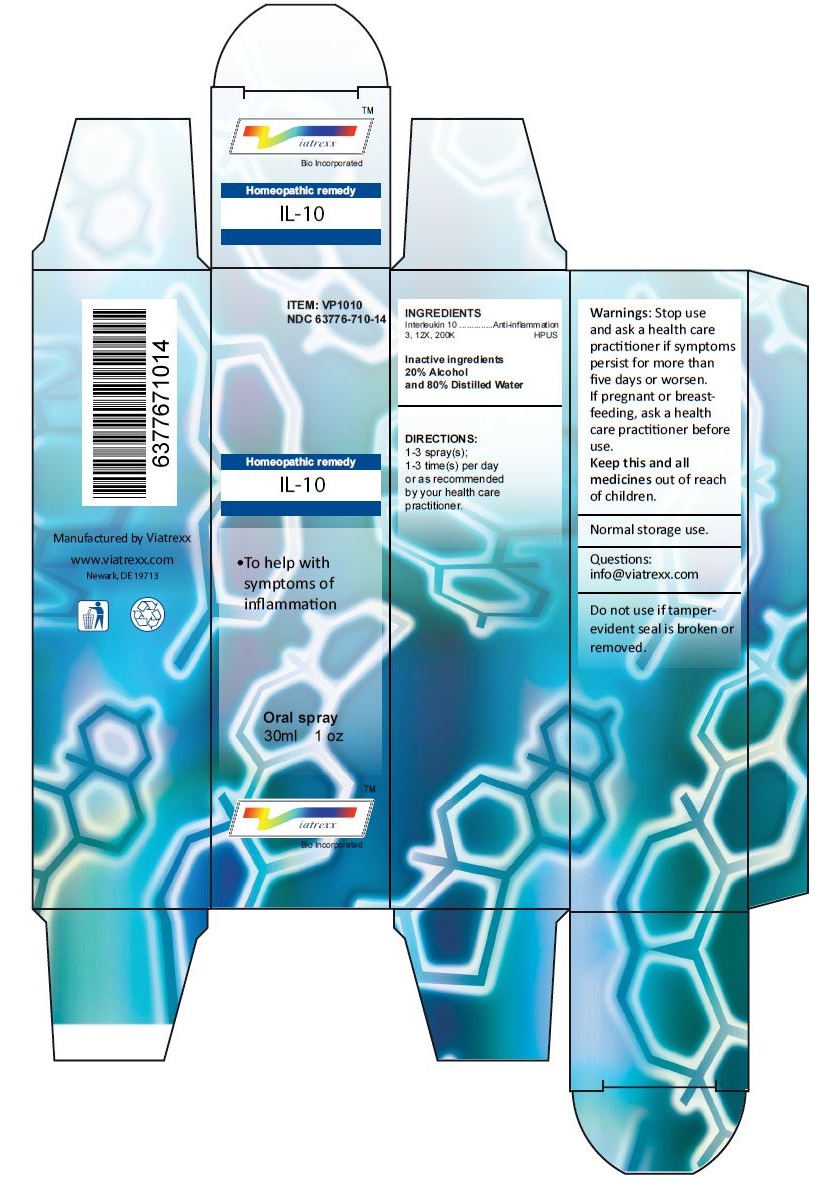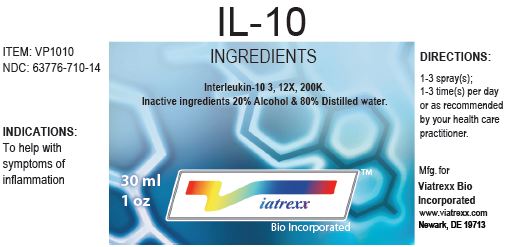 DRUG LABEL: IL-10
NDC: 63776-710 | Form: SPRAY
Manufacturer: VIATREXX BIO INCORPORATED
Category: homeopathic | Type: HUMAN OTC DRUG LABEL
Date: 20221130

ACTIVE INGREDIENTS: INTERLEUKIN-10 200 [kp_C]/1 mL
INACTIVE INGREDIENTS: ALCOHOL; WATER

IL-10

Active Ingredients

Interleukin 10, 3, 12X, 200K

Purpose:

Interleukin 10 | Anti-inflammation

Uses

To help with symptoms of inflammation

Warnings

Stop use and ask a health care practitioner if symptoms persist for more than five days or worsen. If pregnant or breastfeeding, ask a health care practitioner before use.

Dosage

1-3 spray(s); 1-3 time(s) per day or as recommended by your health care practitioner.

KEEP OUT OF REACH OF CHILDREN

Keep this and all medicines out of reach of children.

Other Ingredients

20% Alcohol and 80% Water

Other Information

Normal storage use.
Do not use if tamper-evident seal is broken or removed.

Questions

info@viatrexx.com

Principal Display Panel

ITEM: VP1010
NDC 63776-710-14
Homeopathic remedy
IL-10
• To help with symptoms of inflammation
Oral spray
30ml 1 oz
Viatrexx™ Bio Incorporated
Manufactured by Viatrexx
www.viatrexx.com
Newark, DE 19713

IL-10
30 ml
1 oz
Viatrexx™ Bio Incorporated
ITEM: VP1010
NDC: 63776-710-14
INDICATIONS:
To help with symptoms of inflammation
DIRECTIONS:
1-3 spray(s); 1-3 time(s) per day or as recommended by your health care practitioner.
Mfg. for
Viatrexx Bio Incorporated.
www.viatrexx.com
Newark, DE 19713